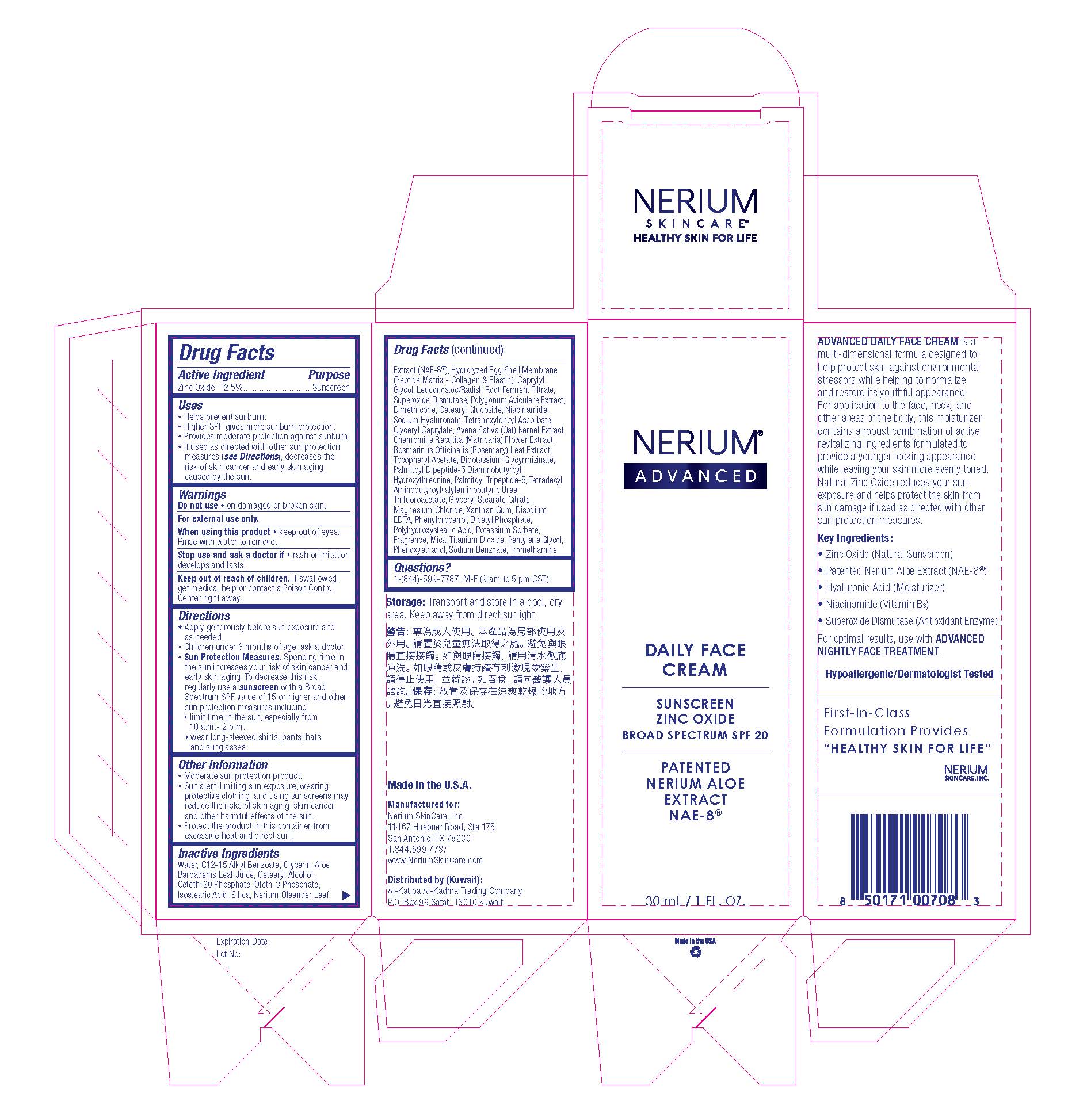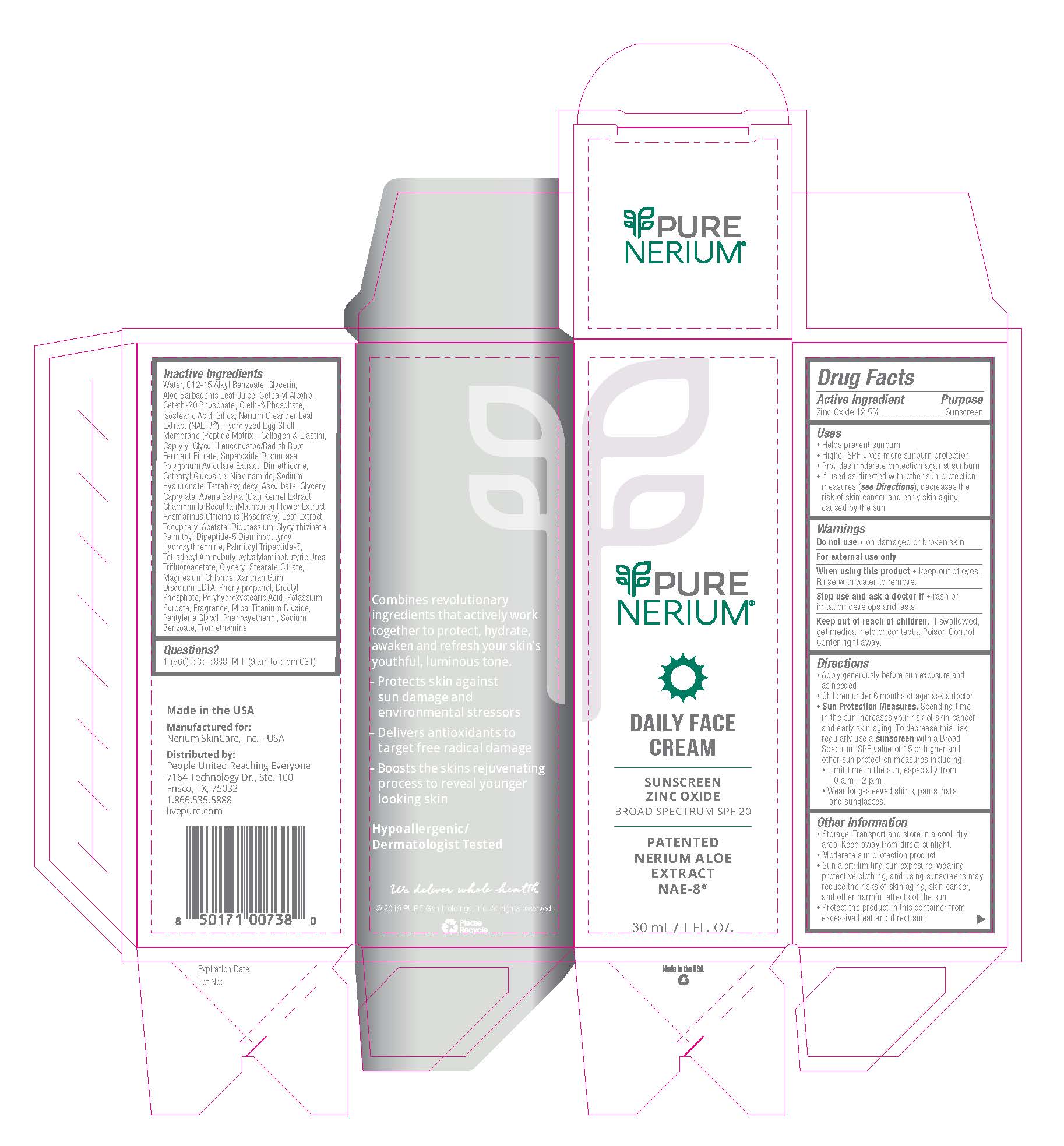 DRUG LABEL: Zinc Oxide
NDC: 10477-1384 | Form: LOTION
Manufacturer: Goodier Cosmetics LLC
Category: otc | Type: HUMAN OTC DRUG LABEL
Date: 20211019

ACTIVE INGREDIENTS: ZINC OXIDE 12.5 g/100 g
INACTIVE INGREDIENTS: WATER; ALKYL (C12-15) BENZOATE; GLYCERIN; ALOE VERA LEAF POLYSACCHARIDES; CETOSTEARYL ALCOHOL; CETETH-20 PHOSPHATE; OLETH-3 PHOSPHATE; ISOSTEARIC ACID; SILICON DIOXIDE; NERIUM OLEANDER LEAF; EGG SHELL MEMBRANE; CAPRYLYL GLYCOL; LEUCONOSTOC/RADISH ROOT FERMENT FILTRATE; SUPEROXIDE DISMUTASE (MN) SACCHAROMYCES CEREVISIAE; POLYGONUM AVICULARE WHOLE; DIMETHICONE; CETEARYL GLUCOSIDE; NIACINAMIDE; HYALURONATE SODIUM; TETRAHEXYLDECYL ASCORBATE; GLYCERYL CAPRYLATE; OAT; MATRICARIA CHAMOMILLA; ROSEMARY; .ALPHA.-TOCOPHEROL ACETATE, DL-; GLYCYRRHIZINATE DIPOTASSIUM; PALMITOYLLYSYLVALYLDIAMINOBUTYROYLTHREONINE; PALMITOYL TRIPEPTIDE-5; TETRADECYL AMINOBUTYROYLVALYLAMINOBUTYRIC UREA TRIFLUOROACETATE; GLYCERYL STEARATE CITRATE; MAGNESIUM CHLORIDE; XANTHAN GUM; DISODIUM ETHYLENEDIAMINEDIACETATE; PHENYLPROPANOL; DIHEXADECYL PHOSPHATE; POLYHYDROXYSTEARIC ACID (2300 MW); POTASSIUM SORBATE; MICA; TITANIUM DIOXIDE; PENTYLENE GLYCOL; PHENOXYETHANOL; SODIUM BENZOATE; TROMETHAMINE

Daily Face Cream Broad Spectrum SPF 20

DAILY FACE
CREAM

SUNSCREEN
ZINC OXIDE
BROAD SPECTRUM SPF 20

PATENTED
NERIUM ALOE
EXTRACT
NAE-8®

Active Ingredient Purpose
Zinc Oxide 12.5%............................Sunscreen

Uses
• Helps prevent sunburn
• Higher SPF gives more sunburn protection
• Provides moderate protection against sunburn
• If used as directed with other sun protection
measures (see Directions), decreases the
risk of skin cancer and early skin aging
caused by the sun

Warnings
For external use only

Do not use • on damaged or broken skin

When using this product • keep out of eyes.
Rinse with water to remove.

Stop use and ask a doctor if • rash or
irritation develops and lasts

Keep out of reach of children. If swallowed,
get medical help or contact a Poison Control
Center right away.

Directions
• Apply generously before sun exposure and as needed
• Children under 6 months of age: ask a doctor
• Sun Protection Measures. Spending time
in the sun increases your risk of skin cancer
and early skin aging. To decrease this risk,
regularly use a sunscreen with a Broad
Spectrum SPF value of 15 or higher and
other sun protection measures including:
• Limit time in the sun, especially from 10 a.m.- 2 p.m.
• Wear long-sleeved shirts, pants, hats and sunglasses.

Other Information
• Storage: Transport and store in a cool, dry
area. Keep away from direct sunlight.
• Moderate sun protection product.
• Sun alert: limiting sun exposure, wearing
protective clothing, and using sunscreens may
reduce the risks of skin aging, skin cancer,
and other harmful effects of the sun.
• Protect the product in this container from
excessive heat and direct sun.

Inactive Ingredients
Water, C12-15 Alkyl Benzoate, Glycerin, Aloe Barbadenis Leaf Juice, Cetearyl Alcohol,
Ceteth-20 Phosphate, Oleth-3 Phosphate, Isostearic Acid, Silica, Nerium Oleander Leaf
Extract (NAE-8®), Hydrolyzed Egg Shell Membrane (Peptide Matrix - Collagen & Elastin),
Caprylyl Glycol, Leuconostoc/Radish Root Ferment Filtrate, Superoxide Dismutase,
Polygonum Aviculare Extract, Dimethicone, Cetearyl Glucoside, Niacinamide, Sodium
Hyaluronate, Tetrahexyldecyl Ascorbate, Glyceryl Caprylate, Avena Sativa (Oat) Kernel Extract,
Chamomilla Recutita (Matricaria) Flower Extract, Rosmarinus Officinalis (Rosemary) Leaf Extract,
Tocopheryl Acetate, Dipotassium Glycyrrhizinate, Palmitoyl Dipeptide-5 Diaminobutyroyl
Hydroxythreonine, Palmitoyl Tripeptide-5, Tetradecyl Aminobutyroylvalylaminobutyric Urea
Trifluoroacetate, Glyceryl Stearate Citrate, Magnesium Chloride, Xanthan Gum,
Disodium EDTA, Phenylpropanol, Dicetyl Phosphate, Polyhydroxystearic Acid, Potassium
Sorbate, Fragrance, Mica, Titanium Dioxide, Pentylene Glycol, Phenoxyethanol, Sodium
Benzoate, Tromethamine

Questions?
1-(866)-535-5888 M-F (9 am to 5 pm CST)

Manufactured for:
Nerium SkinCare, Inc.
San Antonio, TX 78230

PACKAGE LABEL

1floz Pure Daily Face Cream

1floz Advanced Daily Face Cream